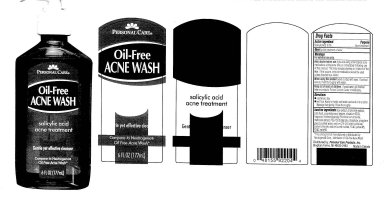 DRUG LABEL: Personal Care Oil-Free Acne Wash
                        
NDC: 29500-7020 | Form: LIQUID
Manufacturer: Personal Care Products, Inc
Category: otc | Type: HUMAN OTC DRUG LABEL
Date: 20111230

ACTIVE INGREDIENTS: SALICYLIC ACID 2.0 mL/100 mL
INACTIVE INGREDIENTS: ALOE; CHAMOMILE; CITRIC ACID MONOHYDRATE; COCAMIDOPROPYL BETAINE; EDETATE DISODIUM; MATRICARIA RECUTITA; PROPYLENE GLYCOL; WATER; SODIUM CHLORIDE; SODIUM LAURETH SULFATE; FD&C YELLOW NO. 5; FD&C RED NO. 40

Personal Care Oil-Free Acne Wash

Active ingredient Purpose

Salicylic acid 2.0 percent Acne treatment

PURPOSE

Uses for the treatment of acne

Warnings

For external use only

Ask a doctor before use if you are using other topical acne medications at the same time

or immediately following use of this product. This may increase dryness or irritation of the skin.

If this occurs, only one medication should be used unless directed by a doctor.

INDICATIONS AND USAGE

Uses for the treatment of acne

Keep out of reach of children. If swallowed, get medical help or contact a Poison Control Center immediately

Directions

use twice a day

wet face, Apply to hands add water and work into a lather

Massage face gently. Rinse thoroughly.

Inactive Ingredients

aloe extract, chamomile extract, citric acid, cocamidopropyl betaine, disodium EDTA,

fragrance, linoleamidopropyl PG- dimonium chloride,

matricaria extract, PEG-150 distearate, phosphate, propylene glycol, purified water,

sodium C14-C16 olefin sulfonate, sodium chloride, sodium laureth sulfate,

FD and C yellow 5, FD and C red 40

DESCRIPTION

This product is not manufactured or distributed by

Neutrogena Corp, distributor of Oil -Free Acne Wash

Distributed by: Personal Care Products, Inc.

Bingham Farms, MI 48025-2463 Made in Canada

PACKAGE LABEL

Personal Care

Oil-Free

Acne Wash

salicylic acid

acne treatment

Gentle yet effective cleanser

Compare to Neutrogena

Oil Free Acne Wash

6 FL OZ (177 mL)